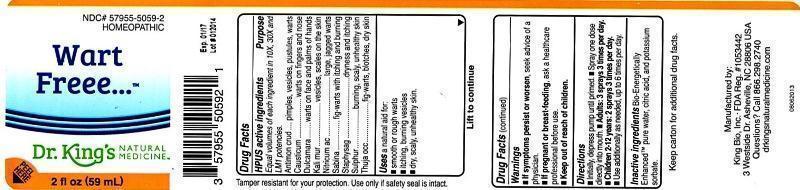 DRUG LABEL: Wart Freee
NDC: 57955-5059 | Form: LIQUID
Manufacturer: King Bio Inc.
Category: homeopathic | Type: HUMAN OTC DRUG LABEL
Date: 20140203

ACTIVE INGREDIENTS: ANTIMONY TRISULFIDE 10 [hp_X]/59 mL; CAUSTICUM 10 [hp_X]/59 mL; SOLANUM DULCAMARA TOP 10 [hp_X]/59 mL; POTASSIUM CHLORIDE 10 [hp_X]/59 mL; NITRIC ACID 10 [hp_X]/59 mL; JUNIPERUS SABINA LEAFY TWIG 10 [hp_X]/59 mL; DELPHINIUM STAPHISAGRIA SEED 10 [hp_X]/59 mL; SULFUR 10 [hp_X]/59 mL; THUJA OCCIDENTALIS LEAFY TWIG 10 [hp_X]/59 mL
INACTIVE INGREDIENTS: WATER; CITRIC ACID MONOHYDRATE; POTASSIUM SORBATE

Wart Freee™

Drug Facts

____________________________________________________________________________________________________________

HPUS active ingredients: Antimonium crudum, Causticum, Dulcamara, Kali muriaticum, Nitricum acidum, Sabina, Staphysagria, Sulphur, Thuja occidentalis.

INDICATIONS AND USAGE

Uses a natural aid for:

- smooth or rough warts
- itching, burning vesicles
- dry, scaly, unhealthy skin

Warnings

- If symptoms persist or worsen, seek advice of a physician.
- If pregnant or breast-feeding, ask a healthcare professional before use.

- Keep out of reach of children.

Directions:

- Initially, depress pump until primed.
- Spray one dose directly into mouth.
- Adults: 3 sprays 3 times per day.
- Children 2-12 years: 2 sprays 3 times per day.
- Use additionally as needed, up to 6 times per day.

INACTIVE INGREDIENT

Inactive ingredients: Bio-Energetically Enhanced™ pure water, citric acid, potassium sorbate.

OTHER SAFETY INFORMATION

Tamper resistant for your protection. Use only if safety seal is intact.

PURPOSE

Uses a natural aid for: •smooth or rough warts •itching •burning vesicles dry, scaly, unhealthy skin